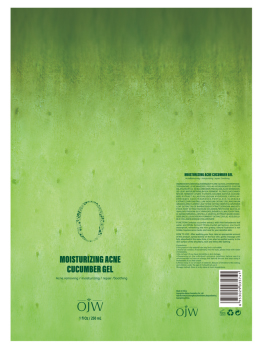 DRUG LABEL: Moisturizing
NDC: 84673-014 | Form: EMULSION
Manufacturer: Guangzhou Meiya Cosmetics Co. ,Ltd.
Category: otc | Type: HUMAN OTC DRUG LABEL
Date: 20241006

ACTIVE INGREDIENTS: ALLANTOIN 250 mg/1 mL
INACTIVE INGREDIENTS: PENTYLENE GLYCOL 0.00024 mg/1 mL; TREHALOSE 0.12 mg/1 mL; BUTYLENE GLYCOL 1 mg/1 mL; SODIUM CHLORIDE 0.000512 mg/1 mL; MALTODEXTRIN 0.00008 mg/1 mL; FARNESOL 0.000011 mg/1 mL; HYDROXYACETOPHENONE 0.35 mg/1 mL; 1,2-HEXANEDIOL 0.3 mg/1 mL; WATER 85.6713 mg/1 mL; SODIUM HYDROXIDE 0.135 mg/1 mL; GLYCERIN 8 mg/1 mL; CAPRYLHYDROXAMIC ACID 0.05 mg/1 mL; FOLIC ACID 0.000002 mg/1 mL; MADECASSOSIDE 0.00001 mg/1 mL; BETAINE 0.12 mg/1 mL

PURPOSE

Function:Contains cucumber extract, with Aloe barbadensis leaf water and Bifida ferment filtrate,crystal gel texture, one touch absorption, refreshing and non-greasy, natural hydration is not Irritate, improve acne marks, and care for your sensitive skin.

INDICATIONS AND USAGE

HOW TO USE : After washing your face, take an appropriate amount of this product, spread evenly on the face skin, gently massage until fully absorbed.At the same time, it can also be applied evenly to the skin surface of the shoulders, neck and limbs after bathing.

WARNINGS

1. This product is for external use only and is not edible;

2. Avoid eye contact, if accidentally into the eyes, please rinse with water immediately;

3. Do not use it if you have dermatitis or skin damage;

4. Depending on the individual's physical condition, before use,It is recommended to have an allergy test behind the ear and stop using it immediately if you feel unwell.

5. Please keep it out of reach of children, Beware of Children's Mis-eating, and children under the age of 3 should not use it.

STOP USE

1. This product is for external use only and is not edible;

2. Avoid eye contact, if accidentally into the eyes, please rinse with water immediately;

3. Do not use it if you have dermatitis or skin damage;

4. Depending on the individual's physical condition, before use,It is recommended to have an allergy test behind the ear and stop using it immediately if you feel unwell.

5. Please keep it out of reach of children, Beware of Children's Mis-eating, and children under the age of 3 should not use it.

DO NOT USE

1. This product is for external use only and is not edible;

2. Avoid eye contact, if accidentally into the eyes, please rinse with water immediately;

3. Do not use it if you have dermatitis or skin damage;

4. Depending on the individual's physical condition, before use,It is recommended to have an allergy test behind the ear and stop using it immediately if you feel unwell.

5. Please keep it out of reach of children, Beware of Children's Mis-eating, and children under the age of 3 should not use it.

KEEP OUT OF REACH OF CHILDREN

Please keep it out of reach of children, Beware of Children's Mis-eating, and children under the age of 3 should not use it.

WHEN USING

1. This product is for external use only and is not edible;

2. Avoid eye contact, if accidentally into the eyes, please rinse with water immediately;

3. Do not use it if you have dermatitis or skin damage;

4. Depending on the individual's physical condition, before use,It is recommended to have an allergy test behind the ear and stop using it immediately if you feel unwell.

5. Please keep it out of reach of children, Beware of Children's Mis-eating, and children under the age of 3 should not use it.